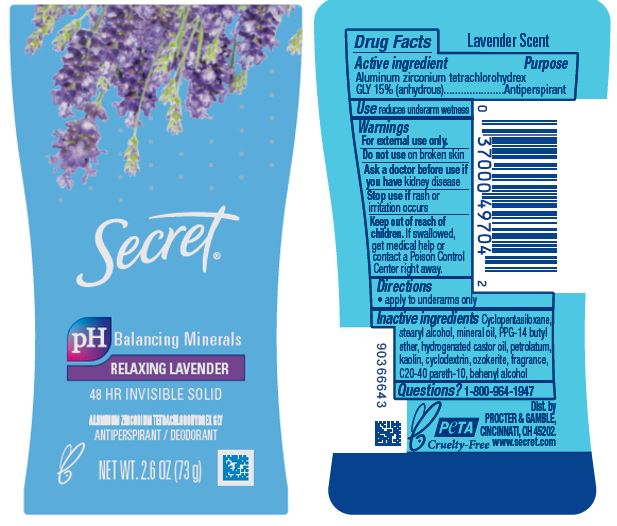 DRUG LABEL: Secret Relaxing Lavender Invisible
NDC: 69423-718 | Form: STICK
Manufacturer: The Procter & Gamble Manufacturing Company
Category: otc | Type: HUMAN OTC DRUG LABEL
Date: 20251231

ACTIVE INGREDIENTS: ALUMINUM ZIRCONIUM TETRACHLOROHYDREX GLY 15 g/100 g
INACTIVE INGREDIENTS: CERESIN; CYCLOPENTASILOXANE; STEARYL ALCOHOL; MINERAL OIL; CYCLODEXTRINS; PETROLATUM; HYDROGENATED CASTOR OIL; PPG-14 BUTYL ETHER; C20-40 PARETH-10; BEHENYL ALCOHOL; KAOLIN

Secret Relaxing Lavender Invisible Solid

Drug Facts

Active ingredient

Aluminum zirconium tetrachlorohydrex Gly 15% (anhydrous)

Purpose

Antiperspirant

Use

reduces underarm wetness

Warnings

For external use only.

Do not use on broken skin

Ask a doctor before use if you have kidney disease

Stop use if rash or irritation occurs

Keep out of reach of children. If swallowed, get medical help or contact a Poison Control Center right away.

Directions

apply to underarms only

Inactive ingredients

Cyclopentasiloxane, stearyl alcohol, mineral oil, PPG-14 butyl ether, hydrogenated castor oil, petrolatum, kaolin, cyclodextrin, ozokerite, fragrance, C20-40 pareth-10, behenyl alcohol

Questions?

1-800-964-1947

www.secret.com

Dist. by PROCTER & GAMBLE,
CINCINNATI, OH 45202.

www.secret.com

PRINCIPAL DISPLAY PANEL - 73 g Canister Label

Secret®

pH Balancing Minerals

RELAXING LAVENDER

48 HR INVISIBLE SOLID

ANTIPERSPIRANT / DEODORANT

ALUMINUM ZIRCONIUM TETRACHLOROHYDREX GLY
NET WT. 2.6 OZ